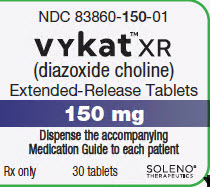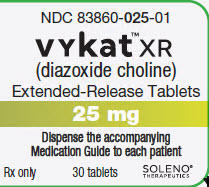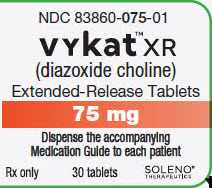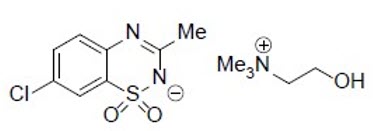 DRUG LABEL: VYKAT XR
NDC: 83860-025 | Form: TABLET, FILM COATED
Manufacturer: Soleno Therapeutics, Inc.
Category: prescription | Type: HUMAN PRESCRIPTION DRUG LABEL
Date: 20250326

ACTIVE INGREDIENTS: diazoxide choline 25 mg/1 1

HIGHLIGHTS OF PRESCRIBING INFORMATION

These highlights do not include all the information needed to use VYKAT XR safely and effectively. See full prescribing information for VYKAT XR.
VYKAT™ XR (diazoxide choline) extended-release tablets, for oral use
Initial U.S. Approval: 1973

1 INDICATIONS AND USAGE

VYKAT XR is indicated for the treatment of hyperphagia in adults and pediatric patients 4 years of age and older with Prader-Willi syndrome (PWS). (1)

2 DOSAGE AND ADMINISTRATION

- Prior to initiation, test fasting plasma glucose and HbA1c; optimize blood glucose in patients who have hyperglycemia. (2.1)
- Do not substitute with diazoxide oral suspension. (2.1)
- Administer orally once daily. (2.2)
- Recommended starting dosage and titration schedule is based on patient’s body weight. (2.2)
  Weight | Starting Dosage | Titration Dosage | Titration Dosage | Target Maintenance Dose
  Weight | Weeks 1 and 2 | Weeks 3 and 4 | Weeks 5 and 6 | Target Maintenance Dose
  20 to <30 kg | 25 mg | 50 mg | 75 mg | 100 mg
  30 to <40 kg | 75 mg | 150 mg | 150 mg | 150 mg
  40 to <65 kg | 75 mg | 150 mg | 225 mg | 225 mg
  65 to <100 kg | 150 mg | 225 mg | 300 mg | 375 mg
  100 to <135 kg | 150 mg | 300 mg | 375 mg | 450 mg
  ≥135 kg | 150 mg | 300 mg | 450 mg | 525 mg
- The maximum recommended dosage is 5.8 mg/kg/day or 525 mg per day. (2.2)
- Interrupt VYKAT XR or reduce dosage for clinically significant elevations in fasting glucose or HbA1c; consider dosage reduction or interruption for clinically significant fluid overload. (2.3)
- See full prescribing information for VYKAT XR dosage modifications due to drug interactions (2.4)
- Following dosage interruption or a missed dose of 7 days or more, re-titrate according to Table 1 or Table 2. (2.5)

3 DOSAGE FORMS AND STRENGTHS

- Extended-release tablets: 25 mg, 75 mg, and 150 mg of diazoxide choline. (3)

4 CONTRAINDICATIONS

- Known hypersensitivity to diazoxide, other components of VYKAT XR, or to thiazides. (4)

5 WARNINGS AND PRECAUTIONS

- Hyperglycemia: Hyperglycemia, including diabetic ketoacidosis, has been reported. During treatment, monitor fasting glucose and HbA1c. Monitor fasting glucose more frequently during first few weeks of treatment in patients with risk factors for hyperglycemia. (2.3, 5.1)
- Risk of Fluid Overload: Edema, including severe reactions associated with fluid overload, has been reported. Monitor for signs or symptoms of edema or fluid overload. (2.3, 5.2)

6 ADVERSE REACTIONS

Most common adverse reactions (incidence ≥10% and at least 2% greater than in placebo) are hypertrichosis, edema, hyperglycemia, and rash. (6)

To report SUSPECTED ADVERSE REACTIONS, contact Soleno Therapeutics, Inc. at 1-833-765-3661 or FDA at 1-800-FDA-1088 or www.fda.gov/medwatch.

7 DRUG INTERACTIONS

- Strong CYP1A2 Inhibitors: Reduce VYKAT XR dosage. (2.4, 7)
- CYP1A2 Substrates: Concomitant use with VYKAT XR is not recommended. (7)
- See full prescribing information for additional clinically significant drug interactions. (7)

8 USE IN SPECIFIC POPULATIONS

- Renal Impairment or Hepatic Impairment: Use is not recommended. (8.6, 8.7)

FULL PRESCRIBING INFORMATION

1 INDICATIONS AND USAGE

VYKAT XR is indicated for the treatment of hyperphagia in adults and pediatric patients 4 years of age and older with Prader-Willi syndrome (PWS).

2 DOSAGE AND ADMINISTRATION

2.1 Important Recommendations Prior to VYKAT XR Initiation

Laboratory Testing Prior to VYKAT XR Initiation

Prior to initiating treatment with VYKAT XR, test fasting plasma glucose (FPG) and HbA1c and optimize blood glucose in patients who have hyperglycemia [see Warnings and Precautions (5.1)].

For fasting glucose and HbA1c monitoring recommendations during VYKAT XR treatment and for dosage modifications based on results, see Dosage and Administration (2.3).

Important Information Regarding Substitution

Do not substitute VYKAT XR with diazoxide oral suspension because the pharmacokinetic profiles are different [see Clinical Pharmacology (12.3)].

2.2 Dosage and Administration Recommendations

Administer VYKAT XR orally with or without food once daily [see Clinical Pharmacology (12.3)].

Swallow tablets whole. Do not split, crush, or chew the extended-release tablets because doing so may compromise the extended-release characteristics, efficacy, or safety of VYKAT XR.

The recommended oral dosage of VYKAT XR is based on body weight. The recommended starting dosage and titration schedule of VYKAT XR are shown in Table 1.

Table 1: Recommended Starting Dosage and Titration Regimen in Adults and Pediatric Patients 4 Years of Age and Older
Weight | Recommended Once Daily Dosage
Weight | Starting Dosage | Titration Dosage | Titration Dosage | Target Maintenance Dose
Weight | Weeks 1 and 2 | Weeks 3 and 4 | Weeks 5 and 6 | Target Maintenance Dose
20 kg to <30 kg | 25 mg | 50 mg | 75 mg | 100 mg
30 kg to <40 kg | 75 mg | 150 mg | 150 mg | 150 mg
40 kg to <65 kg | 75 mg | 150 mg | 225 mg | 225 mg
65 kg to <100 kg | 150 mg | 225 mg | 300 mg | 375 mg
100 kg to <135 kg | 150 mg | 300 mg | 375 mg | 450 mg
≥135 kg | 150 mg | 300 mg | 450 mg | 525 mg

The maximum recommended dosage of VYKAT XR is 5.8 mg/kg/day or 525 mg per day. Dosages above 5.8 mg/kg/day or 525 mg per day have not been evaluated in patients with PWS.

2.3 Monitoring and Dosage Modifications Due to Adverse Reactions

Elevations in Fasting Glucose or HbA1c

After initiating treatment with VYKAT XR, monitor:

- Fasting glucose (FPG or fasting blood glucose) at least once every week for the first 2 weeks, then at least once every 4 weeks, and as clinically indicated.
- HbA1c every 3 months and as clinically indicated.

Monitor fasting glucose more frequently during the first few weeks of VYKAT XR treatment in patients with risk factors for hyperglycemia.

If clinically significant elevations in fasting glucose of HbA1c occur during treatment, temporarily interrupt VYKAT XR or reduce the dosage until glycemic parameters are appropriately managed. Consider initiation or adjustment of standard antidiabetic therapy(ies). If clinically significant glucose elevations are noted during titration, titrate over a longer duration and/or to a lower dosage [see Warnings and Precautions (5.1)].

Fluid Overload

Monitor for signs or symptoms of edema or fluid overload. Consider dosage reduction or temporary dosage interruption in the event of clinically significant fluid overload. If clinically significat fluid overload is noted during titration, titrate over a longer duration and/or to a lower dosage [see Warnings and Precautions (5.2)].

Titration After Resolution of Fluid Overload or Elevation in Fasting Glucose or HbA1c

If fluid overload or elevations in fasting glucose or HbA1c resolve after a dosage reduction:

- For patients weighing less than 30 kg, titrate the dosage in increments of no more than 25 mg every 2 weeks or titrate over longer duration to a maximum dosage of 5.8 mg/kg/day.
- For patients weighing greater than or equal to 30 kg, titrate the dosage in increments of no more than 75 mg every 2 weeks or titrate over longer duration to a maximum dosage of 5.8 mg/kg/day.

For recommendations on resuming VYKAT XR after dosage interruption, see Dosage and Administration (2.5).

2.4 Dosage Modifications for Concomitant Use with Strong CYP1A2 Inhibitors

VYKAT XR dosage modifications for concomitant use with strong CYP1A2 inhibitors are shown in Table 2 [see Drug Interactions (7)].

Table 2: VYKAT XR Dosage Modifications for Concomitant Use with Strong CYP1A2 Inhibitors
Weight | VYKAT XR Recommended Once Daily Dosage
Weight | Starting Dosage | Titration Dosage | Titration Dosage | Target Maintenance Dose
Weight | Weeks 1 and 2 | Weeks 3 and 4 | Weeks 5 and 6 | Target Maintenance Dose
20 to <30 kg | 25 mg | 25 mg | 50 mg | 75 mg
30 to <40 kg | 50 mg | 100 mg | 100 mg | 100 mg
40 to <65 kg | 50 mg | 100 mg | 150 mg | 150 mg
65 to <100 kg | 100 mg | 150 mg | 200 mg | 250 mg
100 to <135 kg | 100 mg | 200 mg | 250 mg | 300 mg
≥135 kg | 100 mg | 200 mg | 300 mg | 325 mg

Based on clinical response, VYKAT XR may be titrated to a maximum recommended dosage of 3.6 mg/kg/day. The VYKAT XR daily dosage should not exceed 325 mg per day.

No dosage modification is recommended when VYKAT XR is concomitantly used with moderate CYP1A2 inhibitors.

2.5 Recommendations Regarding Dosage Interruption, Missed Dose, or Discontinuation of Treatment

Following a dosage interruption or missed dose of:

- Less than 7 days, resume VYKAT XR at the previous dosage
- 7 days or more, re-titrate VYKAT XR according to Table 1 or 2, as appropriate [see Dosage and Administration (2.2, 2.4)]

Treatment with VYKAT XR can be discontinued without tapering.

3 DOSAGE FORMS AND STRENGTHS

Extended-release tablets:

- VYKAT XR 25mg of diazoxide choline: white, capsule-shaped, film-coated, waxed tablets, debossed with S-25 on one side.
- VYKAT XR 75 mg of diazoxide choline: white, round, standard convex-shaped, film-coated, waxed tablets, debossed with S-75 on one side.
- VYKAT XR 150 mg of diazoxide choline: white, oval-shaped, film-coated, waxed tablets, debossed with S-150 on one side.

4 CONTRAINDICATIONS

VYKAT XR is contraindicated in patients with known hypersensitivity to diazoxide, other components of VYKAT XR, or to thiazides. Erythema multiforme has been reported with VYKAT XR [see Adverse Reactions (6)].

5 WARNINGS AND PRECAUTIONS

5.1 Hyperglycemia

VYKAT XR increases blood glucose, due primarily to an inhibition of insulin release from the pancreas. Hyperglycemia, including severe adverse reactions associated with diabetic ketoacidosis, occurred in VYKAT XR-treated patients during clinical trials [see Adverse Reactions (6)].

Precipitating conditions for diabetic ketoacidosis may include reduction in the dosages of concomitant antihyperglycemic medications, increase in the dosages of concomitant growth hormone, intercurrent illness, surgery, volume depletion or alcohol abuse. Signs and symptoms of ketoacidosis include nausea, vomiting, abdominal pain, generalized malaise and shortness of breath.

Before initiating VYKAT XR, test fasting plasma glucose (FPG) and HbA1c; optimize blood glucose in patients who have hyperglycemia. After initiating treatment with VYKAT XR, regularly monitor fasting glucose (FPG or fasting blood glucose) and HbA1c [see Dosage and Administration (2.3)]. Monitor fasting glucose more frequently for the first few weeks of treatment with VYKAT XR in patients with risk factors for hyperglycemia, such as obesity, elevated FPG, HbA1c at the upper limit of normal or above, concomitant use of growth hormone, or concomitant use of systemic corticosteroids.

Advise patients of the signs and symptoms of hyperglycemia (e.g., excessive thirst, urinating more often than usual or higher amount of urine than usual, or increased appetite with weight loss). If a patient experiences hyperglycemia after initiating treatment with VYKAT XR, monitor fasting glucose as clinically indicated, and at least twice weekly until fasting glucose decreases to normal levels. Consider monitoring ketones in patients with worsening hyperglycemia.

If hyperglycemia is treated with anti-hyperglycemic medication during VYKAT XR treatment, continue monitoring fasting glucose at least once a week for 8 weeks, followed by once every 2 weeks and as clinically indicated. Consider consultation with a healthcare provider with expertise in the treatment of hyperglycemia and counsel patients on lifestyle changes. Based on the severity of the hyperglycemia, VYKAT XR may require dosage interruption, reduction, or discontinuation in order to avoid progression to ketoacidosis [see Dosage and Administration (2.3)].

5.2 Risk of Fluid Overload

Edema, including general, localized, and peripheral edema, occurred in 27% of VYKAT XR-treated patients versus 12% of placebo-treated patients in the placebo-controlled trial with treatment-naïve subjects (Study 1). Severe adverse reactions associated with fluid overload, including pulmonary edema, were reported in VYKAT XR-treated patients during clinical trials [see Adverse Reactions (6)].

The antidiuretic property of diazoxide may lead to significant fluid retention, which may precipitate congestive heart failure in patients with compromised cardiac reserve. VYKAT XR has not been studied in patients with compromised cardiac reserve and should be used with caution in these patients.

Monitor for signs or symptoms of edema or fluid overload and consider appropriate clinical management, which may include VYKAT XR dosage reduction or treatment interruption, if clinically significant [see Dosage and Administration (2.3)].

6 ADVERSE REACTIONS

The following clinically significant adverse reactions are discussed in greater detail in other sections of the labeling:

- Hyperglycemia [see Warnings and Precautions (5.1)]
- Risk of Fluid Overload [see Warnings and Precautions (5.2)]

Adverse Reactions from Clinical Studies of VYKAT XR in Patients with PWS

Because clinical trials are conducted under widely varying conditions, adverse reaction rates observed in the clinical trials of a drug cannot be directly compared to rates in the clinical trials of another drug and may not reflect the rates observed in practice.

In the clinical study development program for treatment of hyperphagia in patients aged 4 years and older with PWS, a total of 125 patients received at least 1 dose of VYKAT XR. Patients received dosages of VYKAT XR up to 5.8 mg/kg/day (up to a maximum dosage of 525 mg/day) for up to 4.86 years (median: 3.0 years) in the following studies:

- Study 1: 13-week, randomized, double-blind, placebo-controlled, parallel-arm study in which 126 patients were randomized in a 2:1 ratio to VYKAT XR or placebo and received at least one dose of VYKAT XR.
- Study 2-OLE: A long-term, open-label, maintenance treatment period in 115 patients (mean duration 2.6 years; maximum duration 4.3 years) who had previously been enrolled in Study 1.
- Study 2-RWP: A 16-week, double-blind, placebo-controlled, randomized withdrawal treatment period, in which 77 patients who had completed Study 1 and Study 2-OLE were randomized in a 1:1 ratio to VYKAT XR or placebo [see Clinical Studies (14)].
- Study 3: A long-term, open-label, maintenance study in 77 patients who had completed Study 1 and Study 2-OLE.

Adverse reactions leading to discontinuation in VYKAT XR-treated patients included aggression, diabetes mellitus, fluid retention, hirsutism, hyperglycemia, lower respiratory tract infection, peripheral edema, pulmonary edema, and papular rash.

The primary safety analyses are based on Study 1. The most common adverse reactions (10% or more and at least 2% greater than in placebo) in Study 1 were hypertrichosis, edema, hyperglycemia, and rash.

Table 3 presents adverse reactions that occurred in at least 5% of patients in Study 1 receiving VYKAT XR and 2% more frequently in VYKAT XR-treated patients than placebo.

Table 3: Adverse Reactions Occurring in ≥5% of Patients with PWS Receiving VYKAT XR and at Least 2% Greater than Placebo in Study 1
Adverse Reaction | VYKAT XR (N=84) | Placebo (N=42)
Hypertrichosis | 36% | 14%
Edema [Edema includes peripheral edema, periorbital edema, swelling face, pulmonary edema, and peripheral swelling.] | 27% | 12%
Hyperglycemia [Hyperglycemia includes type 2 diabetes mellitus.] | 17% | 5%
Rash [Rash includes contact dermatitis, erythema multiforme, maculo-papular rash, papular rash, and urticaria.] | 12% | 2%
Pyrexia | 6% | 0%
Arthralgia | 5% | 2%
Influenza | 5% | 2%
Nasopharyngitis | 5% | 2%

In Study 2-RWP, the adverse reactions that occurred most frequently (at least 5%) and to a greater extent than placebo included:

Immune System Disorders: Seasonal allergy

Investigations: Increased weight

Nervous System Disorders: Hyperphagia, anxiety, affect lability, anger, compulsive hoarding, suicidal ideation

Respiratory Disorders: Streptococcal pharyngitis, upper respiratory infection

Skin and Subcutaneous Tissue Disorders: Hirsutism

Erythema multiforme was reported in one subject in Study 1. One subject in Study 3 experienced a serious adverse reaction of diabetic ketoacidosis.

Adverse Reactions from Clinical Trials or Postmarketing Experience of Diazoxide in An Unapproved Population

The following adverse reactions associated with use of diazoxide for an unapproved population have been identified in clinical studies or post-marketing reports. Because some of these reactions were reported voluntarily from a population of uncertain size, it is not always possible to reliably estimate their frequency or establish a causal relationship to drug exposure.

Immune System Disorders: Hypersensitivity

Investigations: Increased serum uric acid, transient neutropenia, thrombocytopenia, decreased hemoglobin/hematocrit, eosinophilia

Respiratory Disorders: Pulmonary hypertension

Special Senses: Cataracts

Musculoskeletal and Connective Tissue Disorders: Abnormal facial features

7 DRUG INTERACTIONS

Table 4 displays clinically significant drug interactions with VYKAT XR.

Table 4: Clinically Significant Drug Interactions with VYKAT XR
Strong CYP1A2 Inhibitors [See www.fda.gov/CYPandTransporterInteractingDrugs for examples of strong CYP1A2 and CYP3A4 inhibitors, sensitive CYP1A2 substrates, and dual strong CYP3A4 / moderate 1A2 inducers.]
Prevention or Management | Reduce the dosage of VYKAT XR when concomitantly used with strong inhibitors of CYP1A2 [see Dosage and Administration (2.4)].
Mechanism and Clinical Effect(s) | VYKAT XR is a CYP1A2 substrate. Concomitant use of VYKAT XR with strong CYP1A2 inhibitors increases exposure of diazoxide, which may increase the frequency and/or severity of adverse reactions from VYKAT XR [see Clinical Pharmacology (12.3)].
CYP1A2 Substrates
Prevention or Management | Concomitant use of VYKAT XR with CYP1A2 substrates is not recommended.
Mechanism and Clinical Effect(s) | VYKAT XR is an inhibitor of CYP1A2. Concomitant use of VYKAT XR with CYP1A2 substrates increases exposure of these substrates. This may increase the frequency and/or severity of adverse reactions from such substrates.
Strong CYP3A4 Inhibitors
Prevention or Management | Monitor the frequency and severity of adverse reactions from VYKAT XR. A dosage reduction of VYKAT XR may be needed when used concomitantly with strong CYP3A4 inhibitors.
Mechanism and Clinical Effect(s) | Concomitant use of VYKAT XR with strong CYP3A4 inhibitors increases exposure of diazoxide, which may increase the frequency and/or severity of adverse reactions from VYKAT XR [see Clinical Pharmacology (12.3)].
Dual Strong CYP3A4 / Moderate 1A2 Inducers
Prevention or Management | Concomitant use of VYKAT XR with dual strong CYP3A4/moderate CYP1A2 inducers is not recommended.
Mechanism and Clinical Effect(s) | VYKAT XR is a substrate of CYP3A4 and CYP1A2. Concomitant use of VYKAT XR with strong CYP3A4/moderate 1A2 inducers may decrease exposure of VYKAT XR. This may decrease the efficacy of VYKAT XR [see Clinical Pharmacology (12.3)].
Drugs Highly Bound to Protein
Prevention or Management | Monitor international normalized ratio (INR) in patients who use coumarin or its derivatives concomitantly with VYKAT XR. Dosage modification of coumarin or its derivatives may be needed when used concomitantly with VYKAT XR. Monitor diphenylhydantoin serum levels when VYKAT XR is used concomitantly with diphenylhydantoin. Dosage modification of diphenylhydantoin may be needed when used concomitantly with VYKAT XR.
Mechanism and Clinical Effect(s) | Diazoxide is highly bound to serum proteins. Diazoxide may displace other drugs which are also highly bound to protein resulting in higher or lower blood levels of the concomitantly used drugs. The impact of protein binding displacement is expected to be clinically important for drugs with narrow therapeutic range such as coumarin or its derivatives and diphenylhydantoin. Protein binding displacement may result in an increased risk of adverse reactions due to higher blood levels of coumarin or its derivative or loss of efficacy due to lower exposures of diphenylhydantoin.
Thiazide or Other Diuretics
Prevention or Management | Monitor for signs and symptoms of hyperglycemia [see Warnings and Precautions (5.1)] and hyperuricemia when VYKAT XR is used concomitantly with thiazides or other diuretics. Dosage adjustment of VYKAT XR or diuretics may be needed when VYKAT XR is concomitantly used with diuretics.
Mechanism and Clinical Effect(s) | Both diazoxide and thiazides or other diuretics may produce hyperglycemia and hyperuricemia. The concomitant use of VYKAT XR with thiazides or other diuretics may potentiate the hyperglycemic and hyperuricemic effects of diazoxide [see Adverse Reactions (6) and Clinical Pharmacology (12.2)].

8 USE IN SPECIFIC POPULATIONS

8.1 Pregnancy

Risk Summary

Available data from case reports with diazoxide use during pregnancy are insufficient to identify a drug-associated risk of major birth defects, miscarriage, or other adverse maternal outcomes.

Adverse reactions, including hyperglycemia, alopecia, and hypertrichosis lanuginosa, have been reported in neonates exposed to diazoxide in utero prior to delivery (see Clinical Considerations).

In animal reproduction studies, oral gavage administration of diazoxide choline to pregnant rats during organogenesis at dose exposures equal to the human exposure of 525 mg resulted in no malformations. Maternal and fetal toxicities were observed at a dose approximately equal to the maximum recommended human dose (MRHD) of 525 mg based on AUC (see Data).

The background risk of major birth defects and miscarriage for the indicated population is unknown. All pregnancies have a background risk of birth defect, loss, or other adverse outcomes. In the US general population, the estimated background risk of major birth defects and miscarriage in clinically recognized pregnancies is 2% to 4% and 15% to 20%, respectively.

Clinical Considerations

Fetal/Neonatal Adverse Reactions

Diazoxide crosses the placenta and has been detected in cord blood. Based on adverse reactions reported in adults, in utero exposure of the infant prior to delivery may produce fetal or neonatal hyperbilirubinemia, thrombocytopenia, altered carbohydrate metabolism, and possibly other adverse reactions. Monitor infants who were exposed to diazoxide in utero for adverse reactions and treat accordingly.

Alopecia and hypertrichosis lanuginosa have occurred in a small number of infants whose mothers received oral diazoxide during the last 19 to 60 days of pregnancy. Abnormal hair growth was first noted at the age of one week and persisted when the infants were last seen at the ages of 5 months to one year. An infant born to a mother who was treated with oral diazoxide, 150 mg daily for 47 days prior to delivery, developed hyperglycemia which resolved after a 6-hour insulin infusion. Because there was an inappropriately low plasma insulin concentration for the degree of hyperglycemia, it was considered compatible with transplacental transfer of diazoxide causing inhibition of release of insulin from the neonatal pancreas.

Labor or Delivery

Intravenous administration of diazoxide during labor may cause cessation of uterine contractions, which may require administration of oxytocic agents to reinstate labor. However, this has not been reported with diazoxide when administered orally. Use caution in administering VYKAT XR during labor.

Data

Animal Data

Diazoxide choline was administered orally to pregnant rats during the period of organogenesis at doses of 40, 100, and 160 mg/kg/day (0.3, 0.6, and 1.2 times the MRHD of 525 mg based on AUC). No malformations were observed; however, decreased fetal body weights, delayed skeletal ossification, and increased fetal resorptions were observed at 160 mg/kg/day (a dose approximately equal to the MRHD based on AUC) which was a maternally toxic dose.

In a study in which rabbits were administered diazoxide intravenously, evidence of skeletal and cardiac teratogenic effects was noted at unknown multiples of the MRHD for diazoxide choline.

8.2 Lactation

Risk Summary

Diazoxide is present in human milk. There are no data on the effects of diazoxide on the breastfed infant or on milk production. The developmental and health benefits of breastfeeding should be considered along with the mother’s clinical need for VYKAT XR and any potential adverse effects on the breastfed child from VYKAT XR or from the underlying maternal condition.

Clinical Considerations

Because of potential adverse reactions, including hyperglycemia, monitoring the infant’s blood glucose may be advisable, especially during the neonatal period.

8.4 Pediatric Use

The safety and effectiveness of VYKAT XR have been established for the treatment of hyperphagia in pediatric patients 4 years of age and older with PWS. Use of VYKAT XR for this indiction is supported by efficacy data from an adequate and well-controlled study that included pediatric patients with PWS [see Clinical Studies (14)] and safety data from additional studies that included pediatric patients with PWS [see Adverse Reactions (6)], and the information on this use is described throughout the labeling.

The safety and effectiveness of VYKAT XR have not been established for the treatment of hyperphagia in pediatric patients with PWS less than 4 years of age.

Adverse Reactions in Pediatric Patients in an Unapproved Population

The following postmarketing adverse reactions have been reported with the use of other diazoxide products for the treatment of hyperinsulinemic hypoglycemia, an unapproved population [see Adverse Reactions (6)]:

- Pulmonary hypertension in pediatric patients less than 6 months of age, including neonates.
- Transient cataracts in association with hyperosmolar coma in a pediatric patient that subsided with correction of the hyperosmolarity.
- Development of abnormal facial features with chronic use in pediatric patients.

VYKAT XR is not approved and is not recommended for the treatment of hyperinsulinemic hypoglycemia.

Juvenile Animal Toxicity Data

Diazoxide choline was orally administered at doses of 29, 58, and 145 mg/kg/day to juvenile rats from weaning (postnatal day 21) through adulthood (postnatal day 91). Reduced body weight and body weight gains, correlated with decreased food consumption, occurred at doses ≥ 58 mg/kg/day. Delayed sexual maturation occurred in males at ≥ 58 mg/kg/day and in females at all doses. Decreased motor activity was observed in males at ≥ 58 mg/kg/day, but no effect was observed on learning and memory at any dose in both males and females. The no adverse effect level (NOAEL) was 29 mg/kg/day, which results in exposures less than the clinical exposure at the maximum recommended human dose (MRHD) of 525 mg based on AUC.

8.5 Geriatric Use

Clinical studies of VYKAT XR did not include any subjects 65 years of age and older to determine whether they respond differently from younger adult subjects.

8.6 Renal Impairment

VYKAT XR has not been studied in patients with renal impairment. VYKAT XR is not recommended in patients with renal impairment.

8.7 Hepatic Impairment

VYKAT XR has not been studied in patients with hepatic impairment. VYKAT XR is not recommended in patients with hepatic impairment.

10 OVERDOSAGE

An overdosage of VYKAT XR may cause marked hyperglycemia, which may be associated with ketoacidosis [see Warnings and Precautions (5.1)].

No specific antidotes for VYKAT XR are known. Monitor ketones in patients with severe hyperglycemia following overdose and consider insulin treatment if necessary. Treat severe hyperglycemia associated with ketoacidosis with prompt insulin administration and restoration of fluid and electrolyte balance. Because of VYKAT XR’s long half-life (approximately 106 hours) in patients with PWS, the symptoms of overdosage (hyperglycemia, with or without ketoacidosis) require prolonged surveillance for periods up to three weeks or until blood sugar levels stabilize within the patient’s normal range. Consider contacting a Poison Help line (1-800-222-1222) or a medical toxicologist for overdosage management recommendations for VYKAT XR.

11 DESCRIPTION

VYKAT XR contains diazoxide choline. Diazoxide choline is very slightly soluble to soluble in solvents dichloromethane, tetrahydrofuran, acetonitrile, and methanol and practically insoluble in solvents methyl tert-butyl ether. The pKa is 8.44 ± 0.01

Diazoxide choline is 7-Chloro-3-methyl-1λ6, 2,4-benzothiadiazin-2-ide 1,1-dioxide 2- hydroxyethyl(trimethyl)azanium. The empirical formula is C8H6ClN2O2S•C5H14NO and the molecular weight is 333.83 g/mole. The structural formula is:

VYKAT XR is for oral administration and is available as extended-release tablets in the following strengths: 25 mg tablet contains diazoxide choline 25 mg, equivalent to 17.2 mg diazoxide; 75 mg tablet contains diazoxide choline 75 mg, equivalent to 51.6 mg diazoxide; and 150 mg tablet contains diazoxide choline 150 mg, equivalent to 103.2 mg diazoxide.

Each tablet contains the following inactive ingredients: carnauba wax, colloidal silicon dioxide, dibasic calcium phosphate dihydrate, hypromellose, magnesium stearate, polyethylene oxide, silicified microcrystalline cellulose, talc, titanium dioxide, and triacetin.

12 CLINICAL PHARMACOLOGY

12.1 Mechanism of Action

The exact mechanism of action of diazoxide choline in the treatment of hyperphagia in patients 4 years of age and older with Prader-Willi syndrome (PWS) is unknown.

12.2 Pharmacodynamics

VYKAT XR resulted in a reduction in fasting plasma insulin from baseline through 1 year of treatment.

Diazoxide increases blood glucose, due primarily to an inhibition of insulin release from the pancreas.

Other pharmacodynamic effects of VYKAT XR include increased uric acid, renin secretion and IgG concentrations, and decreased cortisol secretion.

12.3 Pharmacokinetics

Absorption

Following oral administration, diazoxide choline is hydrolyzed to diazoxide prior to absorption. Peak diazoxide concentrations occur after 16 hours. VYKAT XR is expected to reach steady state after 7 days.

Effect of Food

Following administration of 150 mg diazoxide choline to healthy subjects, the Cmax increased by 39% and AUCinf was unchanged with a high-fat meal, compared to fasted conditions. The median Tmax was 12 hours in the fasted state, and 8 hours in the fed state.

Distribution

The volume of distribution of diazoxide following oral administration is about 44.9 L. Diazoxide is extensively bound (91% to 93%) to plasma proteins (primarily human albumin), and crosses the blood-brain barrier.

Elimination

Metabolism

Diazoxide is mainly metabolized by CYP1A2 and to a minor extent by CYP3A4. Diazoxide is metabolized by oxidation or sulfate conjugation at the methyl group resulting in two inactive metabolites. Following long term administration in patients with PWS, only metabolite M1(3-hydroxymethyl-7-chloro-1,2,4- benzothiadiazine-1,1-dioxide) is detectable in circulation.

Excretion

Diazoxide is excreted almost exclusively in urine as free or conjugated compound. In humans, following administration of radiolabeled diazoxide, 85 to 92% of the total dose was recovered in urine, with about 31% eliminated as unchanged drug. About 2% of the dose is eliminated in the feces. The terminal half-life following single-dose administration in healthy subjects was 28.7 to 32.4 hours. In patients with PWS, the estimated terminal half-life is 106 hours.

Specific Populations

Pediatric Patients

Approximately 72% of the patients with PWS were under 17 years of age at enrollment. There were no clinically relevant differences in pharmacokinetics in these participants compared to those observed in adult participants.

Male and Female Patients

No sex-related differences in pharmacokinetics have been observed in clinical trials of VYKAT XR in patients with PWS who have hyperphagia.

Patients with Renal or Hepatic Impairment

VYKAT XR has not been studied in patients with renal or hepatic impairment [see Use in Specific Populations (8.6, 8.7)].

Drug Interaction Studies

Drugs That Inhibit CYP1A2

VYKAT XR is metabolized by CYP1A2 and coadministration with a strong CYP1A2 inhibitor may increase exposure of diazoxide and decrease concentrations of diazoxide metabolites. In a clinical study with fluvoxamine (a strong CYP1A2 inhibitor), coadministration with fluvoxamine at an inhibitory dose increased single dose diazoxide Cmax by 17.5% and AUC0-inf by 60% compared to the same parameter measured on single dose in the absence of fluvoxamine co-administration [see Drug Interactions (7)].

Strong CYP3A4 Inhibitor

Physiology-based pharmacokinetic model-based analysis suggests that concomitant use of VYKAT XR with itraconazole (a strong CYP3A4 inhibitor) may increase the AUCinf of VYKAT XR by 1.1 to 2-fold, compared to VYKAT XR alone. Itraconazole did not appreciably affect the Cmax of VYKAT XR [see Drug Interactions (7)].

Strong CYP3A4 Inducers

Physiology-based pharmacokinetic model-based analysis suggests that concomitant use of VYKAT XR with rifampin (a strong CYP3A4 inducer and moderate CYP1A2 inducer) may decrease the Cmax and AUCinf of VYKAT XR by 14% to 30% and 40% to 70%, respectively, compared to VYKAT XR alone [see Drug Interactions (7)].

Drugs that Alter Gastric pH

Use of VYKAT XR with gastric pH adjusting-drugs is not expected to affect the pharmacokinetics of diazoxide. Based on population pharmacokinetic modeling, use of VYKAT XR with gastric pH adjusting drugs did not significantly affect relative bioavailability or apparent clearance of diazoxide.

Protein Binding Displacement

VYKAT XR may also displace bilirubin bound to serum protein, thus resulting in higher blood levels of bilirubin.

In Vitro Studies

Enzyme systems: Diazoxide choline is an inhibitor of CYP1A2. It is not an inhibitor of CYP2B6, 2C19, 2C8, 2C9, 2D6 or 3A4. It does not induce CYP1A2, CYP2B6 or CYP3A4 at the therapeutic dose range.

Transporter systems: Diazoxide choline is a substrate for OAT1, OAT3, and BCRP. It is an inhibitor of OAT1/3. It is not an inhibitor of P-gp, BCRP, MATE1/2-K, OATP1B1/3, OCT1/2 at the therapeutic dose range.

13 NONCLINICAL TOXICOLOGY

13.1 Carcinogenesis, Mutagenesis, Impairment of Fertility

Carcinogenesis

Carcinogenicity studies have not been performed with diazoxide choline.

Mutagenesis

Diazoxide choline was not mutagenic in the in vitro bacterial reverse mutation assay (Ames test) and in the mouse lymphoma assay. Diazoxide choline was not clastogenic in the in vivo rat micronucleus assay.

Impairment of Fertility

Diazoxide choline was orally administered to male and female rats at doses of 58, 116, and 232 mg/kg/day (1, 2, and 4 times the maximum recommended human dose (MRHD) on a mg/m^2 basis). Females were treated two weeks prior to mating and continuing through conception and implantation and males were treated for four weeks prior to mating continuing for 35 days after mating. No effects on male or female fertility parameters were observed. Decreases in the mean number of corpora lutea, implantation sites, and live embryos occurred at 4 times the MRHD on a mg/m^2 basis.

13.2 Animal Toxicology and/or Pharmacology

Cataracts were observed in dogs given repeated daily oral doses of diazoxide of approximately 40 mg/kg/day for one month. The lenticular changes resembled those which occur experimentally in animals with increased blood glucose levels.

14 CLINICAL STUDIES

The efficacy of VYKAT XR for the treatment of hyperphagia in adults and pediatric patients ages 4 years and older with PWS was established in a 16-week, double-blind, placebo-controlled, randomized withdrawal study period (Study 2-RWP; NCT03714373) that followed an open-label study period of VYKAT XR. During Study 2-RWP, 77 patients with hyperphagia and PWS were randomized in a 1:1 ratio to continue their current oral dosage using a weight-based dosage regimen of VYKAT XR or placebo [see Dosage and Adminstration (2.2)]. Prior to participating in Study 2-RWP, patients received double-blind and/or open-label VYKAT XR for a mean duration of 3.3 years (range 2.5 to 4.5 years; Study 1 and Study 2-OLE). Results from Study 2-RWP are presented below.

Demographic and baseline disease characteristics were similar for the VYKAT XR and placebo groups. The mean age was 14.9 years of age (range 7 to 29 years of age). Most of the participants were White (86%), 7% were Black or African American, and 8% were of multiple races. The majority of participants were non-Hispanic (91%) and female (56%).

The primary efficacy endpoint was the Change from Baseline in the Hyperphagia Questionnaire for Clinical Trials (HQ-CT) Total Score at Week 16. The HQ-CT is a 9-item, observer-reported outcome measure that assesses a range of hyperphagic and food-related behaviors during the prior 2 weeks. An item score of 0 indicates an absence of behaviors, with a score of 4 indicating the most frequent or severe behaviors. The HQ-CT Total Score may range from 0 to 36, with higher scores indicating greater overall severity of hyperphagic and food-related behaviors.

At the end of the 16-week randomized withdrawal study period, there was statistically significant worsening of hyperphagia in the placebo group relative to the VYKAT XR group, as assessed by the HQ- CT Total Score (see Table 5).

Table 5: Study 2-RWP HQ-CT Total Score, Least Square Mean Change from Baseline to the End of the Randomized Withdrawal Period (Week 16) in Patients with Hyperphagia and PWS
Treatment Group | Number of Patients | Mean Baseline Score (SD) | LS Mean Change from Baseline (SE) | LS Mean Difference [VYKAT XR - placebo] (95% CI)
VYKAT XR | 38 | 9.0 (6.3) | 2.6 (1.1) | -5.0 (-8.1, -1.8)
Placebo | 39 | 8.1 (5.1) | 7.6 (1.1) | -5.0 (-8.1, -1.8)
CI, confidence interval; HQ-CT, Hyperphagia Questionnaire for Clinical Trials; LS Mean, least squares mean; RWP, randomized withdrawal period; SD, standard deviation; SE, standard error

16 HOW SUPPLIED/STORAGE AND HANDLING

How Supplied

VYKAT XR is supplied as follows:

Strength | Description | Package Configuration | NDC Number
25 mg diazoxide choline | White, capsule-shaped tablets, debossed with "S-25" on one side | 30-count bottles | 83860-025-01
75 mg diazoxide choline | White, round, standard convex tablets, debossed with "S-75" on one side | 30-count bottles | 83860-075-01
150 mg diazoxide choline | White, oval-shaped tablets, debossed with “S-150” on one side. | 30-count bottles | 83860-150-01

Storage and Handling

Store at 20°C to 25°C (68°F to 77°F); excursions permitted between 15° and 30°C (59° and 86°F) [see USP Controlled Room Temperature].

Keep in tightly closed container. Protect from humidity. Do not remove desiccant.

17 PATIENT COUNSELING INFORMATION

Advise the patient to read the FDA-approved patient labeling (Medication Guide).

Administration Instructions

Advise patients to swallow tablets whole and not to split, crush, or chew VYKAT XR [see Dosage and Administration (2.2)].

Hyperglycemia

Advise the patient or caregiver that VYKAT XR can cause hyperglycemia, sometimes leading to diabetic ketoacidosis, and that the patient will have monitoring of blood glucose before and during VYKAT XR treatment. Advise patients or caregivers on the signs and symptoms of hyperglycemia (e.g., excessive thirst, urinating more often than usual or higher amount of urine than usual, or increased appetite with weight loss) and ketoacidosis (e.g., nausea, vomiting, abdominal pain, generalized malaise and shortness of breath) and to contact their healthcare provider if these signs or symptoms occur [see Warnings and Precautions (5.1)].

Risk of Fluid Overload

Advise the patient or caregiver that VYKAT XR may cause edema, including severe adverse reactions associated with fluid overload. Advise patients or caregivers on the signs and symptoms of edema and to contact their healthcare provider if signs or symptoms of edema occur [see Warnings and Precautions (5.2)].

Manufactured for:
Soleno Therapeutics, Inc.
100 Marine Parkway, Suite 400
Redwood City, CA 94065
© 2025 Soleno Therapeutics, Inc. All rights reserved.

MEDICATION GUIDE
VYKAT™ XR (vye kat ex ar)
(diazoxide choline)
extended-release tablets, for oral use

What is the most important information I should know about VYKAT XR?
VYKAT XR may cause serious side effects, including:

- High blood sugar levels (hyperglycemia). Hyperglycemia is common during treatment with VYKAT XR and can also be severe. Hyperglycemia can lead to a condition called diabetic ketoacidosis (increased ketones in the blood) in some people who take VYKAT XR. Diabetic ketoacidosis is a serious condition that needs to be treated in a hospital and can be life-threatening.
  Your healthcare provider will:
  - check your blood sugar levels before you start VYKAT XR, at least 1 time every week for the first 2 weeks of treatment, then at least 1 time every 4 weeks and as needed during treatment.
  - check your blood sugar more often during the first few weeks of treatment if you have an increased chance of getting hyperglycemia.
  - check your HbA1c, which is another measurement of blood sugar control, before starting treatment, then 1 time every 3 months and as needed during treatment.
  If you get hyperglycemia during treatment with VYKAT XR, your healthcare provider may:
  - give you medicines to treat hyperglycemia or change your dose if you already take them
  - change your dose, temporarily stop, or permanently stop VYKAT XR
  Tell your healthcare provider if you get any of the following signs and symptoms:
  - hyperglycemia
    - feel very thirsty
    - need to urinate more often than usual
    - have higher amounts of urine than usual
    - feel more hungry than usual
    - weight loss
  - diabetic ketoacidosis
    - nausea
    - vomiting
    - stomach-area (abdominal) pain
    - feel weak or very tired
    - trouble breathing
- Too much fluid in your body (fluid overload). Swelling in the body (edema) from too much fluid is common during treatment with VYKAT XR and can also be severe. Your healthcare provider may decrease your dose or temporarily stop VYKAT XR if you get fluid overload. Tell your healthcare provider if you have trouble breathing or get any other signs or symptoms of fluid overload such as swelling of your legs, ankles, or feet, or unusual swelling anywhere in your body.

What is VYKAT XR?
VYKAT XR is a prescription medicine used to treat extreme hunger, constant thoughts about food, and constant urge to eat that cannot be satisfied with food (hyperphagia) in adults and children 4 years of age and older with Prader-Willi syndrome (PWS). It is not known if VYKAT XR is safe and effective in children under 4 years of age.

Who should not take VYKAT XR?
Do not take VYKAT XR if you are allergic to diazoxide, any ingredients in VYKAT XR, or medicines called thiazides. See the end of this Medication Guide for a complete list of ingredients in VYKAT XR.

Before taking VYKAT XR, tell your healthcare provider about all of your medical conditions, including if you:

- have diabetes or prediabetes
- are sick
- plan to have surgery
- drink alcohol very often
- are dehydrated or have lost a lot of body fluid
- have heart problems or a history of swelling in your legs or other parts of your body
- have liver or kidney problems
- re pregnant, or plan to become pregnant. VYKAT XR may harm your unborn baby. Tell your healthcare provider right away if you become pregnant during treatment with VYKAT XR.
- are breastfeeding or plan to breastfeed. VYKAT XR passes into your breast milk, and it is not known if it can harm your baby. Tell your healthcare provider if you plan to breastfeed during treatment with VYKAT XR.

Tell your healthcare provider about all of the medicines you take, including prescription and over-the-counter medicines, vitamins, and herbal supplements. Taking VYKAT XR with certain other medicines may affect the way VYKAT XR or the other medicine works and may increase your risk of side effects.
Do not change your dose or stop any medicines you take or start any new medicines without talking to your healthcare provider first during treatment with VYKAT XR. Know the medicines you take. Keep a list of them to show your healthcare provider and pharmacist when you get a new medicine.
Especially tell your healthcare provider if you take:

- medicines to lower blood sugar
- growth hormones
- corticosteroids
- diuretics (water pills)
- phenytoin
- warfarin

How should I take VYKAT XR?

- Take VYKAT XR exactly as your healthcare provider tells you to take it. Your healthcare provider will decide how much VYKAT XR you will take and may slowly increase your dose when you first start taking VYKAT XR.
- Take VYKAT XR by mouth 1 time per day with or without food.
- Swallow VYKAT XR tablets whole. Do not split, crush, or chew the tablets.
- You should not miss a dose of VYKAT XR. If you miss a dose of VYKAT XR, take the missed dose as soon as you remember. Do not take 2 doses of VYKAT XR at the same time to make up for a missed dose. If you missed a dose of VYKAT XR and did not remember to take another dose, call your healthcare provider to discuss what you should do next.
- The dose of VYKAT XR is not the same as diazoxide oral suspension. Do not change between VYKAT XR and diazoxide oral suspension products.

If you take too much VYKAT XR, call your healthcare provider or Poison Help Line at 1-800-222-1222 or go to the nearest hospital emergency room right away.

What are the possible side effects of VYKAT XR?

- See "What is the most important information I should know about VYKAT XR?"

The most common side effects of VYKAT XR also include:

- increased hair growth all over the body
- rash

These are not all of the possible side effects of VYKAT XR. Call your doctor for medical advice about side effects. You may report side effects to FDA at 1-800-FDA-1088.

How should I store VYKAT XR?

- Store VYKAT XR at room temperature between 68°F to 77°F (20°C to 25°C).
- Close the bottle tightly after each dose.
- Keep VYKAT XR tablets dry (protect from humidity).
- The bottle contains a desiccant to help keep the tablets dry. Keep the desiccant in the VYKAT XR bottle.

Keep VYKAT XR and all medicines out of the reach of children.

General information about the safe and effective use of VYKAT XR.
Medicines are sometimes prescribed for purposes other than those listed in a Medication Guide. Do not use VYKAT XR for a condition for which it was not prescribed. Do not give VYKAT XR to other people, even if they have the same symptoms that you have. It may harm them. You can ask your pharmacist or healthcare provider for information about VYKAT XR that is written for health professionals.

What are the ingredients in VYKAT XR?
Active ingredient: diazoxide choline
Inactive ingredients: carnauba wax, colloidal silicon dioxide, dibasic calcium phosphate dihydrate, hypromellose magnesium stearate, polyethylene oxide, silicified microcrystalline cellulose, talc, titanium dioxide, and triacetin.
Manufactured for: Soleno Therapeutics, Inc., 100 Marine Parkway, Suite 400, Redwood City, CA 94065
For more information, call 1-833-765-3661.

This Medication Guide has been approved by the U.S. Food and Drug Administration.

Issued: 3/2025

Bottle Label - VYKAT XR - 25 mg
PRINCIPAL DISPLAY PANEL

NDC 83860-025-01
Vykat™ XR
(diazoxide choline)
Extended-Release Tablets
25 mg
Dispense the accompanying
Medication Guide to each patient
Rx only 30 tablets SOLENO®THERAPEUTICS

Bottle Label - VYKAT XR - 75 mg
PRINCIPAL DISPLAY PANEL

NDC 83860-075-01
Vykat™ XR
(diazoxide choline)
Extended-Release Tablets
75 mg
Dispense the accompanying
Medication Guide to each patient
Rx only 30 tablets SOLENO®THERAPEUTICS

Bottle Label - VYKAT XR - 150 mg
PRINCIPAL DISPLAY PANEL

NDC 83860-150-01
Vykat™ XR
(diazoxide choline)
Extended-Release Tablets
150 mg
Dispense the accompanying
Medication Guide to each patient
Rx only 30 tablets SOLENO®THERAPEUTICS